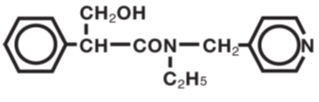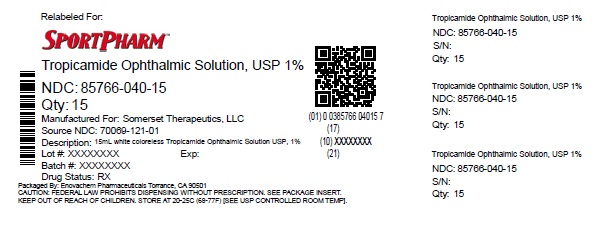 DRUG LABEL: Tropicamide
NDC: 85766-040 | Form: SOLUTION/ DROPS
Manufacturer: Sportpharm LLC
Category: prescription | Type: HUMAN PRESCRIPTION DRUG LABEL
Date: 20260206

ACTIVE INGREDIENTS: TROPICAMIDE 10 mg/1 mL
INACTIVE INGREDIENTS: BENZALKONIUM CHLORIDE; SODIUM CHLORIDE; EDETATE DISODIUM; SODIUM HYDROXIDE; HYDROCHLORIC ACID; WATER

Tropicamide Ophthalmic Solution, USP 1%
Somerset Therapeutics, LLC

DESCRIPTION

Tropicamide Ophthalmic Solution, USP is an anticholinergic prepared as a sterile topical ophthalmic solution. The active ingredient is represented by the chemical structure:

Established name:

Tropicamide ophthalmic solution, USP

Chemical name:

Benzeneacetamide, N-ethyl-α-(hydroxymethyl)- N-(4-pyridinylmethyl).

Each mL contains: Active:tropicamide 1%. Preservative:benzalkonium chloride 0.01%. Inactives:sodium chloride, edetate disodium, hydrochloric acid and/or sodium hydroxide (to adjust pH), Water for injection. pH range 4.0 - 5.8.

CLINICAL PHARMACOLOGY

This anticholinergic preparation blocks the responses of the sphincter muscle of the iris and the ciliary muscle to cholinergic stimulation, dilating the pupil (mydriasis). The stronger preparation (1%) also paralyzes accommodation. This preparation acts in 15-30 minutes, and the duration of activity is approximately 3-8 hours. Complete recovery from mydriasis in some individuals may require 24 hours. The weaker strength may be useful in producing mydriasis with only slight cycloplegia. Heavily pigmented irides may require more doses than lightly pigmented irides.

INDICATIONS AND USAGE

For mydriasis and cycloplegia for diagnostic procedures.

CONTRAINDICATIONS

Contraindicated in persons showing hypersensitivity to any component of this preparation.

WARNINGS

FOR TOPICAL OPHTHALMIC USE ONLY. NOT FOR INJECTION.

This preparation may cause CNS disturbances which may be dangerous in pediatric patients. The possibility of psychotic reactions and behavioral disturbances due to hypersensitivity to anticholinergic drugs should be considered.

Mydriatics may produce a transient elevation of intraocular pressure.

Remove contact lenses before using.

PRECAUTIONS

General

The lacrimal sac should be compressed by digital pressure for two to three minutes after instillation to reduce excessive systemic absorption.

Information for Patients

Do not touch dropper tip to any surface, as this may contaminate the solution. Patient should be advised not to drive or engage in potentially hazardous activities while pupils are dilated. Patient may experience sensitivity to light and should protect eyes in bright illumination during dilation. Parents should be warned not to get this preparation in their child's mouth and to wash their own hands and the child's hands following administration.

Drug Interactions

Tropicamide may interfere with the antihypertensive action of carbachol, pilocarpine, or ophthalmic cholinesterase inhibitors.

Carcinogenesis, Mutagenesis, Impairment of Fertility

There have been no long-term studies done using tropicamide in animals to evaluate carcinogenic potential.

Pregnancy

Animal reproduction studies have not been conducted with tropicamide. It is also not known whether tropicamide can cause fetal harm when administered to a pregnant woman or can affect reproduction capacity. Tropicamide should be given to a pregnant woman only if clearly needed.

Nursing Mothers

It is not known whether this drug is excreted in human milk. Because many drugs are excreted in human milk, caution should be exercised when tropicamide is administered to a nursing woman.

Pediatric Use

Tropicamide may rarely cause CNS disturbances which may be dangerous in pediatric patients. Psychotic reactions, behavioral disturbances, and vasomotor or cardiorespiratory collapse in children have been reported with the use of anticholinergic drugs (See WARNINGS). Keep this and all medications out of the reach of children.

Geriatric Use

No overall differences in safety or effectiveness have been observed between elderly and younger patients.

ADVERSE REACTIONS

Ocular:Transient stinging, blurred vision, photophobia and superficial punctuate keratitis have been reported with the use of tropicamide. Increased intraocular pressure has been reported following the use of mydriatics.

Non-Ocular:Dryness of the mouth, tachycardia, headache, allergic reactions, nausea, vomiting, pallor, central nervous system disturbances and muscle rigidity have been reported with the use of tropicamide. Psychotic reactions, behavioral disturbances, and vasomotor or cardiorespiratory collapse in children have been reported with the use of anticholinergic drugs.

DOSAGE AND ADMINISTRATION

For refraction, instill one or two drops of 1% solution in the eye(s), repeated in five minutes. If patient is not seen within 20 to 30 minutes, an additional drop may be instilled to prolong mydriatic effect. Individuals with heavily pigmented irides may require higher strength or more doses. Mydriasis will reverse spontaneously with time, typically in 4 to 8 hours. However, in some cases, complete recovery may take up to 24 hours.

HOW SUPPLIED

Tropicamide Ophthalmic Solution USP, 1% (15 mL) filled in 15 mL Natural LDPE Bottle and natural LDPE nozzles with red colored HDPE caps.

NDC 85766-040-15 (relabeled from NDC 70069-121-01)

STORAGE:Store at 8°C to 27°C (46°F-80°F). Do not refrigerate or store at high temperatures. Avoid freezing. Keep container tightly closed.

Rx only

Distributed by:

Sportpharm LLC
379 Van Ness Ave 1401,
Torrance, CA 90501

Relabeled by:

Enovachem PHARMACEUTICALS

Torrance, CA 90501